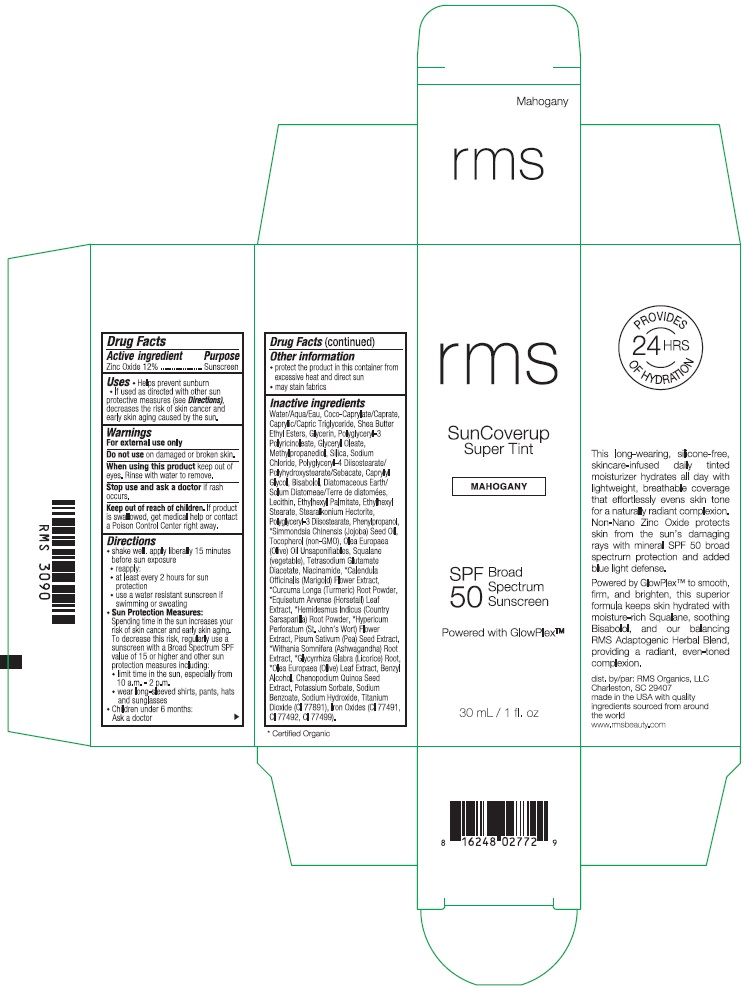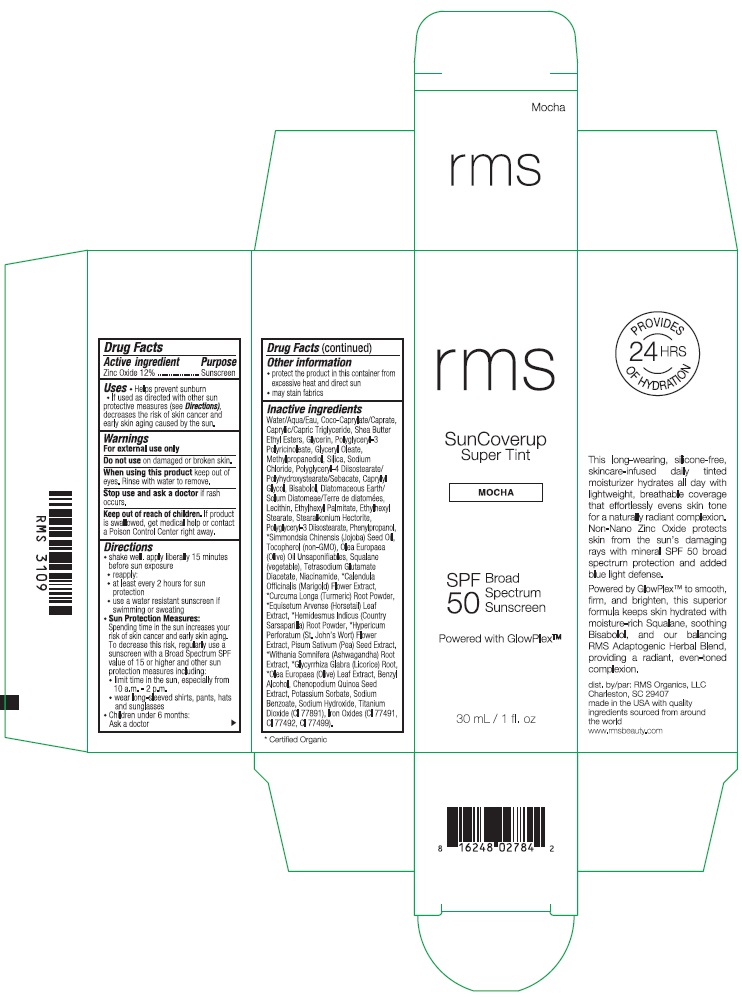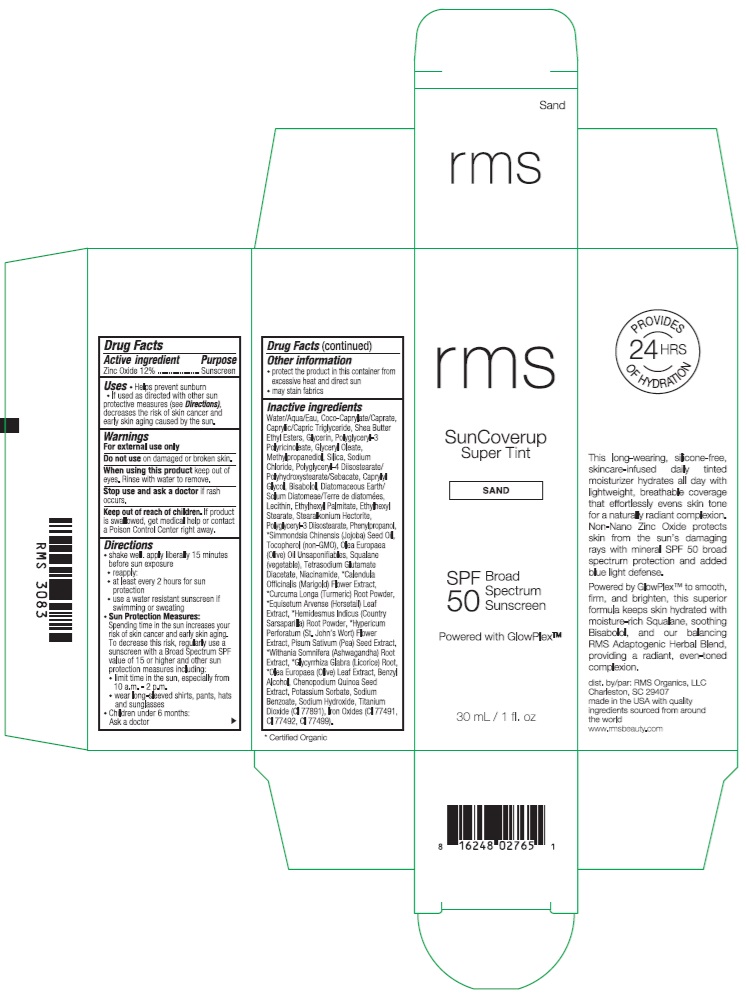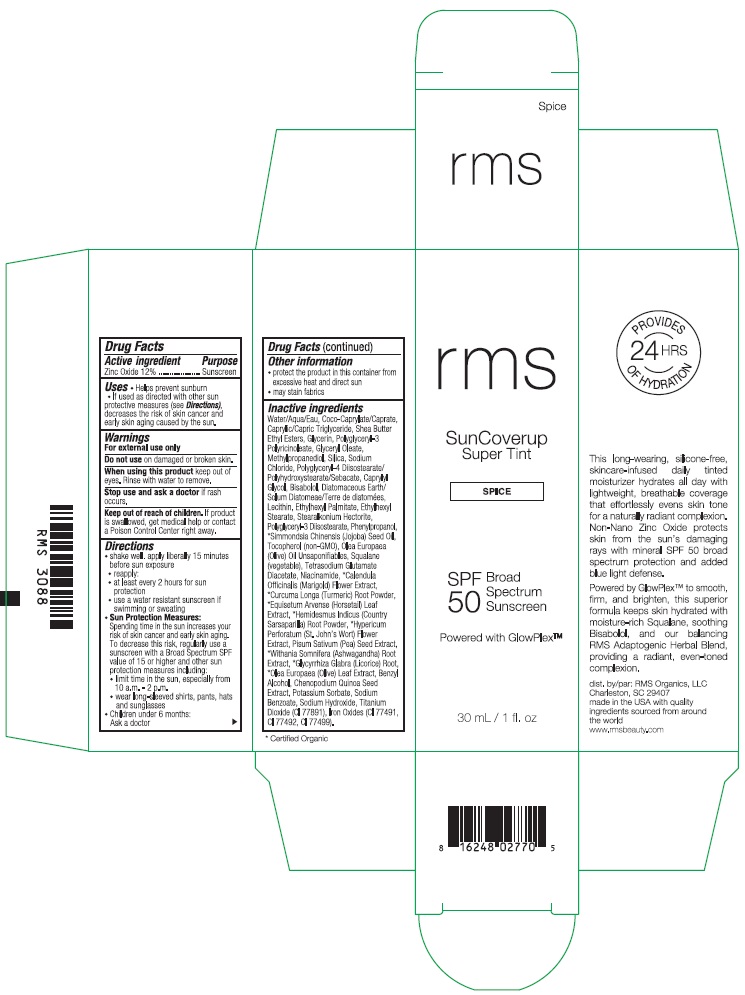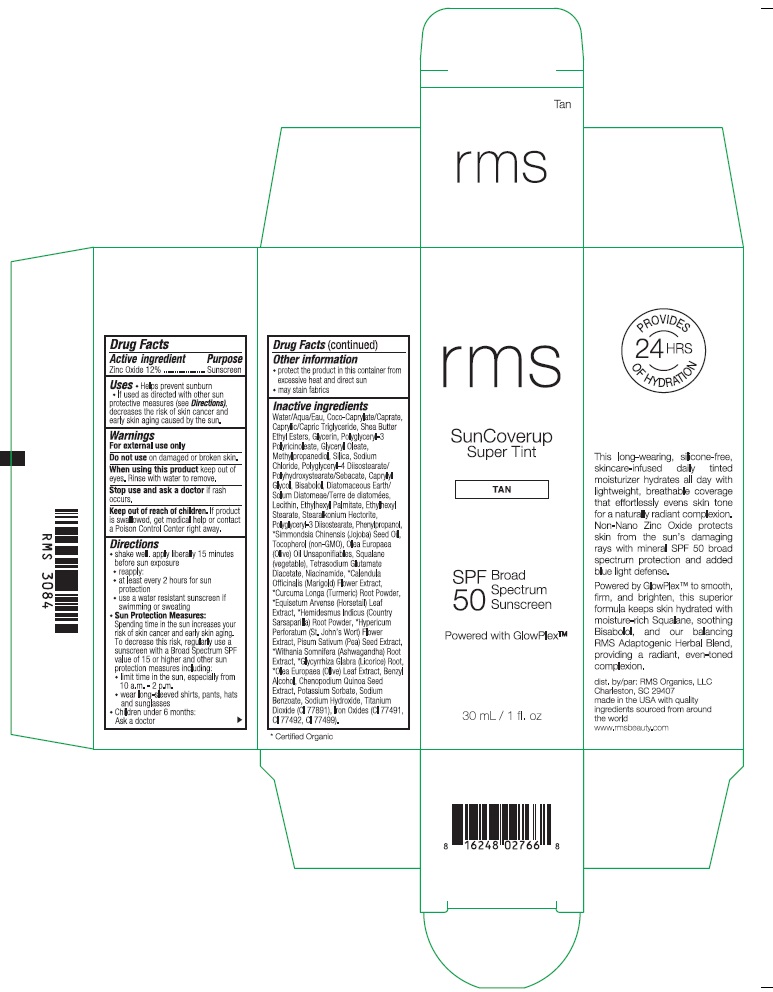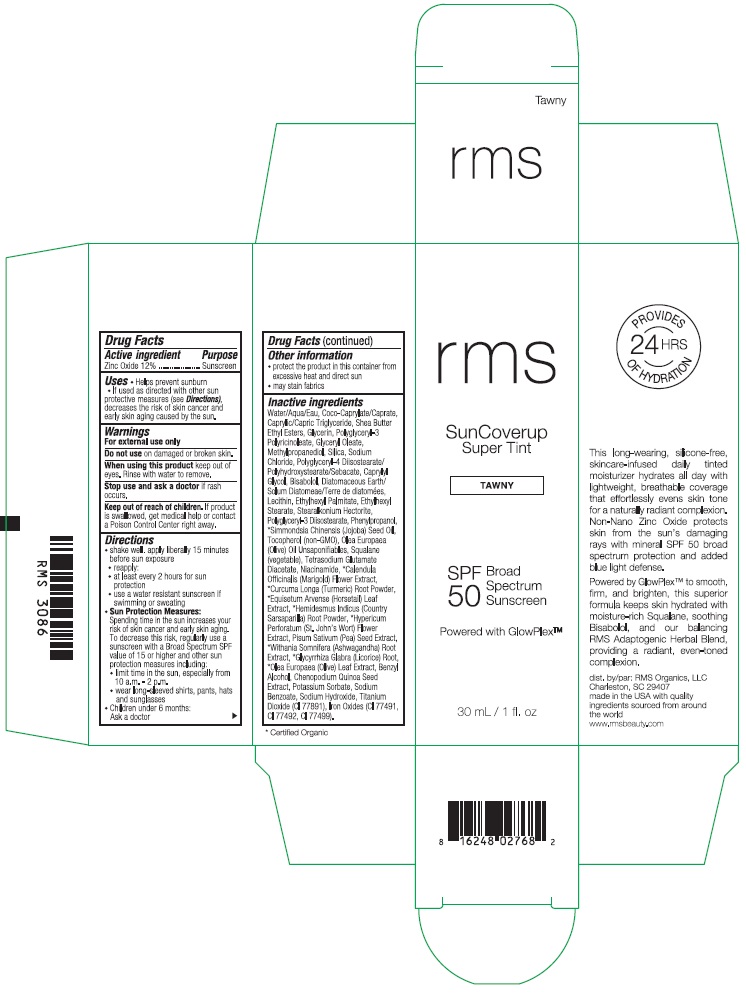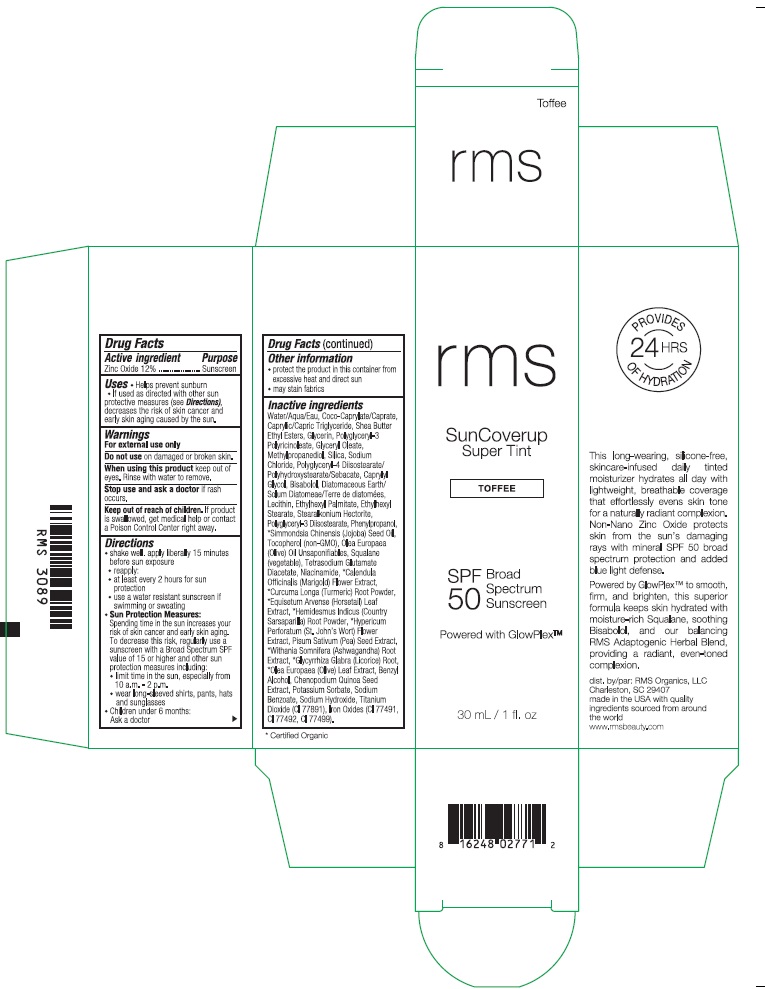 DRUG LABEL: RMS SUNCOVERUP SUPER TINT SPF 50 TAWNY
NDC: 83249-015 | Form: LOTION
Manufacturer: Rms organics LLC
Category: otc | Type: HUMAN OTC DRUG LABEL
Date: 20240604

ACTIVE INGREDIENTS: ZINC OXIDE 120 mg/1 mL
INACTIVE INGREDIENTS: POLYGLYCERYL-3 PENTARICINOLEATE; POLYGLYCERYL-4 DIISOSTEARATE/POLYHYDROXYSTEARATE/SEBACATE; LECITHIN, SUNFLOWER; SHEA BUTTER ETHYL ESTERS; ETHYLHEXYL PALMITATE; SQUALANE; OLEA EUROPAEA (OLIVE) OIL UNSAPONIFIABLES; FERRIC OXIDE RED; CALENDULA OFFICINALIS FLOWER; HYPERICUM PERFORATUM FLOWER; GLYCYRRHIZA GLABRA; STEARALKONIUM HECTORITE; MEDIUM-CHAIN TRIGLYCERIDES; COCO-CAPRYLATE/CAPRATE; METHYLPROPANEDIOL; POLYGLYCERYL-3 DIISOSTEARATE; TURMERIC; SODIUM CHLORIDE; LEVOMENOL; SILICON DIOXIDE; TOCOPHEROL; POTASSIUM SORBATE; DIATOMACEOUS EARTH; FERROSOFERRIC OXIDE; GLYCERIN; WATER; TETRASODIUM GLUTAMATE DIACETATE; FERRIC OXIDE YELLOW; EQUISETUM ARVENSE BRANCH; HEMIDESMUS INDICUS ROOT; WITHANIA SOMNIFERA ROOT; OLEA EUROPAEA LEAF; JOJOBA OIL; CAPRYLYL GLYCOL; ETHYLHEXYL STEARATE; PHENYLPROPANOL; NIACINAMIDE; SODIUM HYDROXIDE; BENZYL ALCOHOL; TITANIUM DIOXIDE; PEA; CHENOPODIUM QUINOA SEED; SODIUM BENZOATE

RMS SUNCOVERUP SUPER TINT SPF 50

Active ingredient

Zinc Oxide 12%

Purpose

Sunscreen

Uses

- Helps prevent sunburn
- If used as directed with other sun protective measures (see Directions), decreases the risk of skin cancer and early skin aging caused by the sun.

Warnings

For external use only.

Do not use

on damaged or broken skin.

When using this product

keep out of eyes. Rinse with water to remove.

Stop use and ask a doctor

if rash occurs.

Keep out of reach of children.

If product is swallowed, get medical help or contact a Poison Control Center right away.

Directions

- shake well. apply liberally 15 minutes before sun exposure
- reapply: at least every 2 hours for sun protection
- use a water resistant sunscreen if swimming or sweating
- Sun Protection Measures: Spending time in the sun increases your risk of skin cancer and early skin aging. To decrease this risk, regularly use a sunscreen with a Broad Spectrum SPF value of 15 or higher and other sun protection measures including:
- limit time in the sun, especially from 10 a.m. - 2 p.m.
- wear long-sleeved shirts, pants, hats and sunglasses
- Children under 6 months: Ask a doctor

Other information

- protect the product in this container from excessive heat and direct sun
- may stain fabrics

Inactive ingredients

Water/Aqua/Eau, Coco-Caprylate/Caprate, Caprylic/Capric Triglyceride, Shea Butter Ethyl Esters, Glycerin, Polyglyceryl-3 Polyricinoleate, Glyceryl Oleate, Methylpropanediol, Silica, Sodium Chloride, Polyglyceryl-4 Diisostearate/Polyhydroxystearate/Sebacate, Caprylyl Glycol, Bisabolol, Diatomaceous Earth/Solum Diatomeae/Terra de diatomees, Lecithin, Ethylhexyl Palmitate, Ethylhexyl Stearate, Stearalkonium Hectorite, Polyglyceryl-3 Diisostearate, Phenylpropanol, *Simmondsia Chinensis (Jojoba) Seed Oil, Tocopherol (non-GMO), Olea Europaea (Olive) Oil Unsaponifiables, Squalane (vegetable), Tetrasodium Glutamate Diacetate, Niacinamide, *Calendula Officinalis (Marigold) Flower Extract, *Curcuma Longa (Turmeric) Root Powder, *Equisetum Arvense (Horsetail) Leaf Extract, *Hemidesmus Indicus (Country Sarsaparilla) Root Powder, *Hypericum Perforatum (St. John's Wort) Flower Extract, Pisum Sativum (Pea) Seed Extract, *Withania Somnifera (Ashwagandha) Root Extract, *Glycyrrhiza Glabra (Licorice) Root, *Olea Europaea (Olive) Leaf Extract, Benzyl Alcohol, Chenopodium Quinoa Seed Extract, Potassium Sorbate, Sodium Benzoate, Sodium Hydroxide, Titanium Dioxide (CI 77891), Iron Oxides (CI 77491, CI 77492, CI 77499).

*Certified Organic

Company Information

dist. by/par: RMS Organics, LLC

Charleston, SC 29407

made in the USA with quality ingredients sourced from around the world

www.rmsbeauty.com